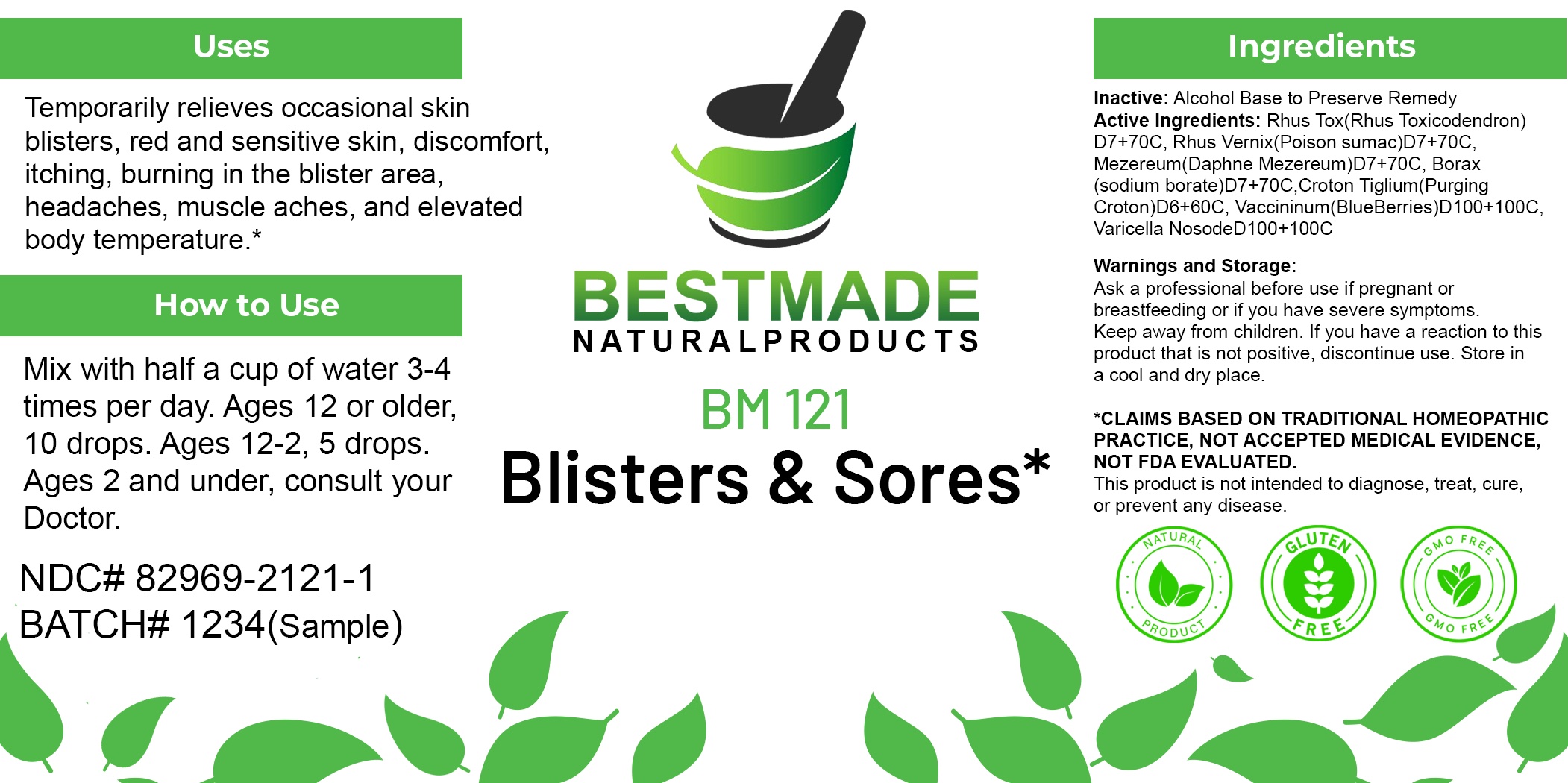 DRUG LABEL: Bestmade Natural Products BM121
NDC: 82969-2121 | Form: LIQUID
Manufacturer: Bestmade Natural Products
Category: homeopathic | Type: HUMAN OTC DRUG LABEL
Date: 20250207

ACTIVE INGREDIENTS: CROTON TIGLIUM SEED 30 [hp_C]/30 [hp_C]; TOXICODENDRON VERNIX LEAFY TWIG 30 [hp_C]/30 [hp_C]; TOXICODENDRON PUBESCENS LEAF 30 [hp_C]/30 [hp_C]; DAPHNE MEZEREUM BARK 30 [hp_C]/30 [hp_C]; SODIUM BORATE 30 [hp_C]/30 [hp_C]; ARSENIC TRIOXIDE 30 [hp_C]/30 [hp_C]
INACTIVE INGREDIENTS: ALCOHOL 30 [hp_C]/30 [hp_C]

BM121

DOSAGE AND ADMINISTRATION

How to Use

Mix with half a cup of water 3-4 times per day. Ages 12 or older, 10 drops. Ages 12-2, 5 drops. Ages 2 and under, consult your Doctor.

Inactive:

Alcohol Base to Preserve Product

ACTIVE INGREDIENTS

Arsenic album D8+80C 0.10mL each (HPUS), Borax D8+80C 0.10mL each (HPUS), Croton tiglium D7+70C 0.10mL each (HPUS), Mezereum D7+70C 0.10mL each (HPUS), Rhus tox D7+70C 0.10mL each (HPUS), Rhus vernix D6+30C 0.10mL each (HPUS)

Uses
Temporarily relieves occasional skin blisters, red and sensitive skin, discomfort itching, burning in the blister area. headaches, muscle aches, and elevated body temperature.*

Uses
Temporarily relieves occasional skin blisters, red and sensitive skin, discomfort itching, burning in the blister area. headaches, muscle aches, and elevated body temperature.*

KEEP OUT OF REACH OF CHILDREN

Warnings and Storage:

Ask a professional before use if pregnant or breastfeeding or if you have severe symptoms.

Keep away from children. If you have a reaction to this product that is not positive, discontinue use. Store in a cool and dry place

*CLAIMS BASED ON TRADITIONAL HOMEOPATHIC PRACTICE, NOT ACCEPTED MEDICAL EVIDENCE NOT FDA EVALUATED.
This product is not intended to diagnose, treat, cure, or prevent any disease.

Warnings and Storage:

Ask a professional before use if pregnant or breastfeeding or if you have severe symptoms.

Keep away from children. If you have a reaction to this product that is not positive, discontinue use. Store in a cool and dry place

*CLAIMS BASED ON TRADITIONAL HOMEOPATHIC PRACTICE, NOT ACCEPTED MEDICAL EVIDENCE NOT FDA EVALUATED.
This product is not intended to diagnose, treat, cure, or prevent any disease.

Entire package label